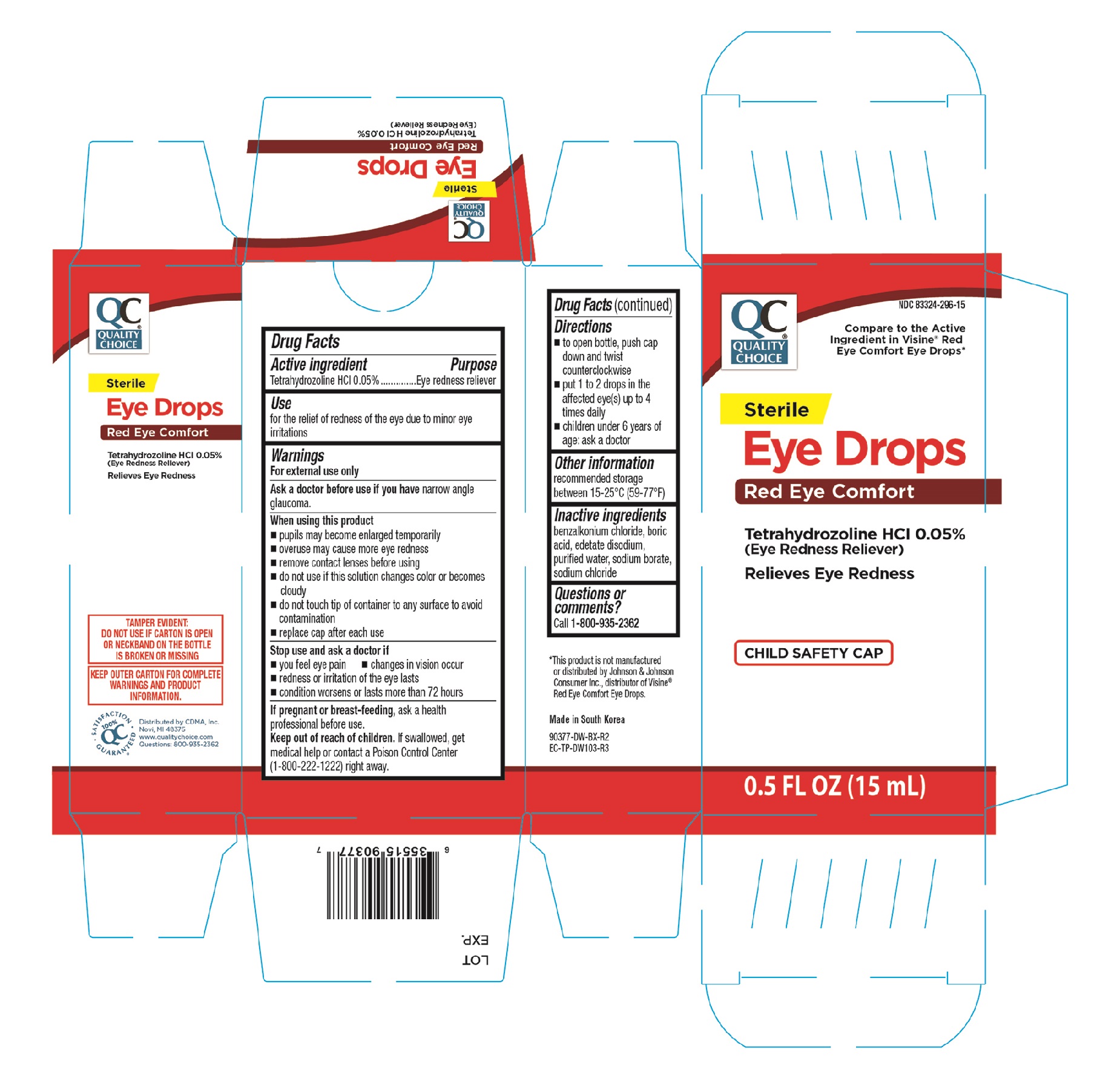 DRUG LABEL: QC Sterile Red Eye
NDC: 83324-296 | Form: SOLUTION/ DROPS
Manufacturer: Chain Drug Marketing Association, Inc.
Category: otc | Type: HUMAN OTC DRUG LABEL
Date: 20251031

ACTIVE INGREDIENTS: TETRAHYDROZOLINE HYDROCHLORIDE 0.5 mg/1 mL
INACTIVE INGREDIENTS: SODIUM BORATE; EDETATE DISODIUM; BENZALKONIUM CHLORIDE; WATER; SODIUM CHLORIDE; BORIC ACID

QC Eye Drops, Original 0.5oz (NBE Visine Original) 90377

Active ingredient Purpose

Tetrahydrozoline HCI 0.05%...........................................Eye redness reliever

Use

for the relief of redness of the eye due to minor eye irritations

Warnings

For external use only

Ask a doctor before use if you have narrow angle glaucoma

When using this product

- pupils may become enlarged temporarily
- overuse may cause more eye redness
- remove contact lenses before using
- do not use if this solution changes color or becomes cloudy
- do not touch tip of container to any surface to avoid contamination
- replace cap after each use

Stop use and ask a doctor if

- you feel eye pain
- changes in vision occur
- redness or irritation of the eye lasts
- condition worsens or lasts more than 72 hours

PREGNANCY OR BREAST FEEDING

If pregnant or breast-feeding, ask a health professional before use.

Keep out of reach of children. If swallowed, get medical help or contact a Poison Control Center (1-800-222-1222) right away.

Directions

- to open bottle, push cap down and twist counterclockwise
- put 1 to 2 drops in the affected eye(s) up to 4 times daily
- children under 6 years of age: ask a doctor

Other information

recommended storage between 15-25°C (59-77°F)

Inactive ingredients

benzalkonium chloride, boric acid, edetate disodium, purified water, sodium borate, sodium chloride

DOSAGE AND ADMINISTRATION

Distributed by:

CDMA, Inc.

Novi, MI 48375

Made in South Korea